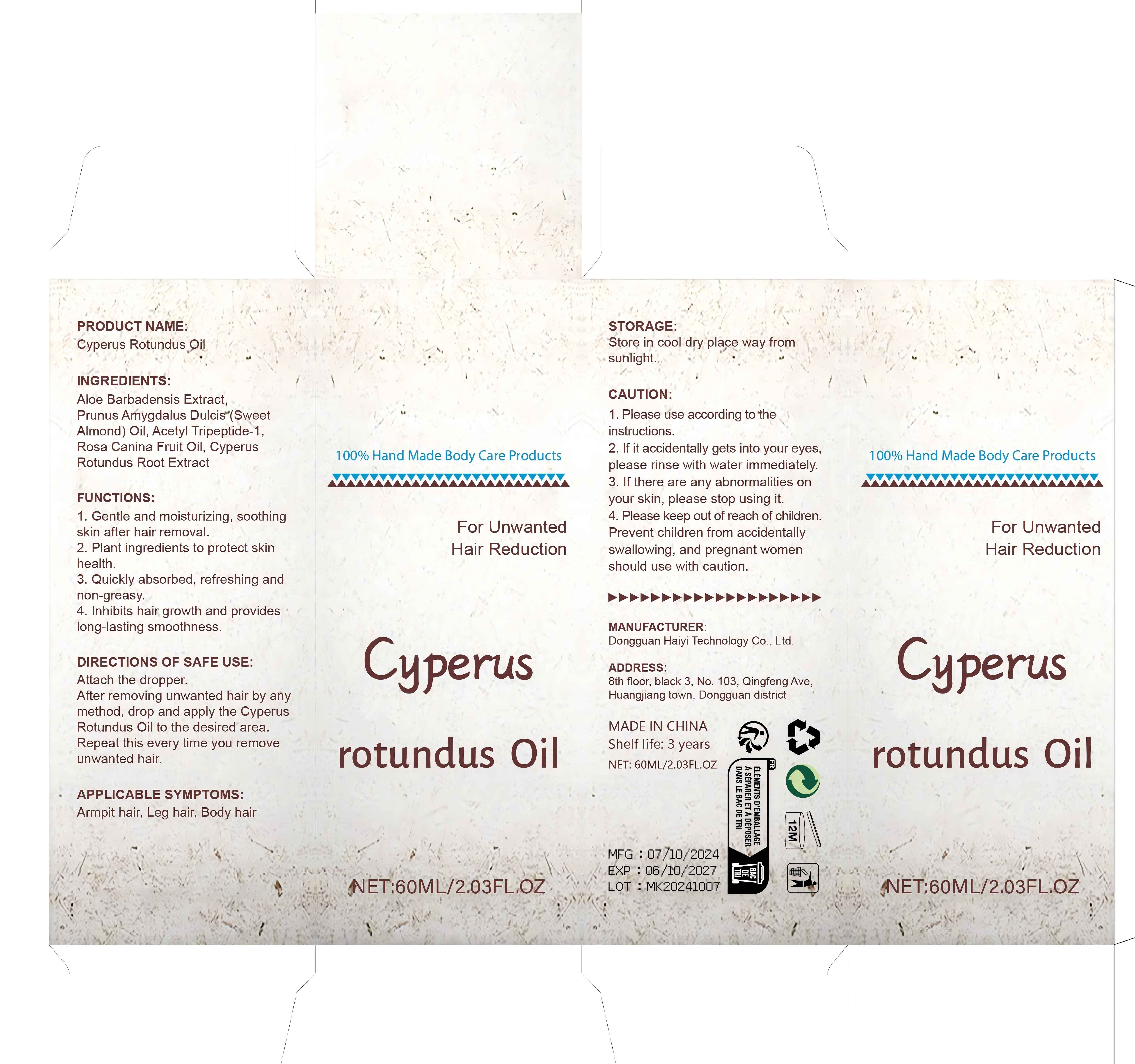 DRUG LABEL: Cyperys Rotundus Oil
NDC: 84732-054 | Form: OIL
Manufacturer: Dongguan Haiyi Technology Co.,Ltd.
Category: otc | Type: HUMAN OTC DRUG LABEL
Date: 20241020

ACTIVE INGREDIENTS: ALOE VERA LEAF 1 mg/60 mL
INACTIVE INGREDIENTS: CYPERUS ROTUNDUS TUBER; ROSA CANINA FRUIT OIL; N-ACETYL DIPEPTIDE-1; ALMOND OIL

Active ingredient

Aloe Barbadensis Extract

Inactive ingredient

Prunus Arygdalus Dulcis(SweetAlmond) Oil, Acetyl Tripeptide-1,Rosa Canina Fruit Oil, Cyperus Rotundus Root Extract

Purpose section

1. Gentle and moisturizing, soothingskin after hair removal.

2. Plant ingredients to protect skinhealth.
3. Quickly absorbed, refreshing andnon-greasy.

4.Inhibits hair growth and provideslong-lasting smoothness

Warning

1. Please use according to theinstructions.

2. lf it accidentally gets into your eyes,please rinse with water immediately.

3. lf there are any abnormalities onyour skin, please stop using it.

4. Please keep out of reach of children.Prevent children from accidentallyswallowing, and pregnant womenshould use with caution.

stop use

This product may cause allergic reactions in asmall number of people.
lf youexperience any discomfort,please stop using it immediately.

not use

Not suitable for use by children, pregnantor breast feeding people.

OUT OF CHILDREN

KEEP THE PRODUCT OUT OF REACH OF CHILDREN to

HOW TO USE

Attach the dropper.After removing unwanted hair by anymethod, drop and apply the CyperusRotundus Oil to the desired area.Repeat this every time you removeunwanted hair.

Dosage

take an appropriateamount,Use 2-3 times a week